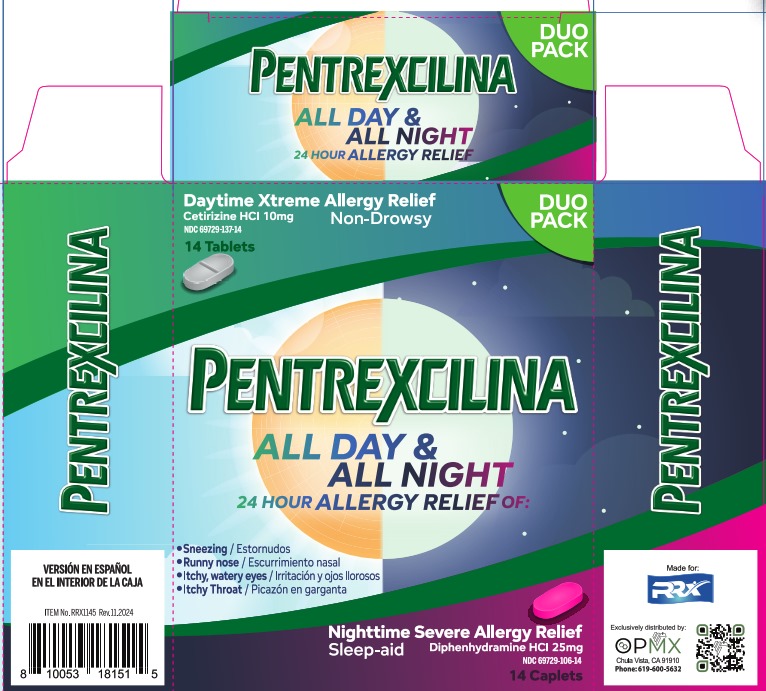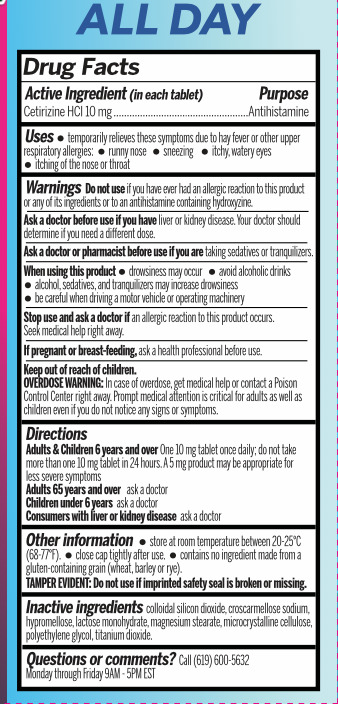 DRUG LABEL: Pentrexcilina Day time
NDC: 69729-137 | Form: TABLET
Manufacturer: OPMX LLC
Category: otc | Type: HUMAN OTC DRUG LABEL
Date: 20241115

ACTIVE INGREDIENTS: CETIRIZINE HYDROCHLORIDE 10 mg/1 1
INACTIVE INGREDIENTS: MICROCRYSTALLINE CELLULOSE; POLYETHYLENE GLYCOL, UNSPECIFIED; LACTOSE MONOHYDRATE; CROSCARMELLOSE SODIUM; HYPROMELLOSE, UNSPECIFIED; TITANIUM DIOXIDE; SILICON DIOXIDE; MAGNESIUM STEARATE

Pentrexcilina Day time

Drug Facts

Active Ingredient

Active Ingredient (in each tablet) | Purpose
Cetirizine HCl 10 mg | Antihistamine

Purpose

Antihistamine

Uses

temporarily relieves these symptoms due to hay fever or other upper respiratory allergies:

- runny nose
- sneezing
- itchy, watery eyes
- itching of the nose or throat

Warnings

Do not use

if you have ever had an allergic reaction to this product or any of its ingredients or to an antihistamine containing hydroxyzine

Ask a doctor before use if you have

Liver or kidney disease. Your doctor should determine if you need a different dose.

Ask a doctor or pharmacist before use if you are

taking sedatives or tranquilizers.

When using this product

- drowsiness may occur
- avoid alcoholic drinks
- alcohol, sedatives, and tranquilizers may increase drowsiness
- be careful when driving a motor vehicle or operating machinery

Stop use and ask a doctor if

an allergic reaction to this product occurs. Seek medical help right away.

If pregnant or breast-feeding,

ask a health professional before use.

Keep out of reach of children.

OVERDOSE WARNING:

In case of overdose, get medical help or contact a Poison Control Center right away. Prompt medical attention is critical for adults as well as children even if you do not notice any signs or symptoms.

Directions

Adults & Children 6 years and over One 10mg tablet once daily; do not take more than one 10mg tablet in 24 hours. A 5 mg product may be appropriate for less severe symptoms

Adults 65 years and over ask a doctor

Children under 6 years ask a doctor

Consumers with liver or kidney disease ask a doctor

Other information

tore at room temperature between 20-25°C (68-77°F).

close cap tightly after use.

contains no ingredients made from a gluten-containing grain (wheat, barley or rye).

TAMPER EVIDENT: Do not use if imprinted safety seal is broken or missing

Inactive ingredients

colloidal silicon dioxide, croscarmellose sodium, hypromellose, lactose monohydrate, magnesium stearate, microcrystalline cellulose, polyethylene glycol, titanium dioxide.

Questions or comments?

Call (619) 600-5632

Monday through Friday 9 AM- 5 PM EST

PACKAGE LABEL

Daytime Xtreme Allergy Relief

Cetirizine HCl 10mg

Non-Drowsy

NDC 69729-137-14

14 Tablets

DUO PACK

PENTREXCILINA

ALL DAY & ALL NIGHT

24 HOUR ALLERGY RELIEF OF:

- Sneezing/ Estornudos
- Runny nose/ Escurrimiento nasal
- Itchy, watery eyes/ Irritación y ojos llorosos
- Itchy throat/ Picazón en garganta

Nighttime Severe Allergy Relief

Sleep-aid

Diphenhydramine HCl 25mg

NDC 69729-106-14

14 Caplets

Made for RRX

Exclusively distributed by:

OPMX

Chula Vista CA 91910

Phone: 619-600-5632